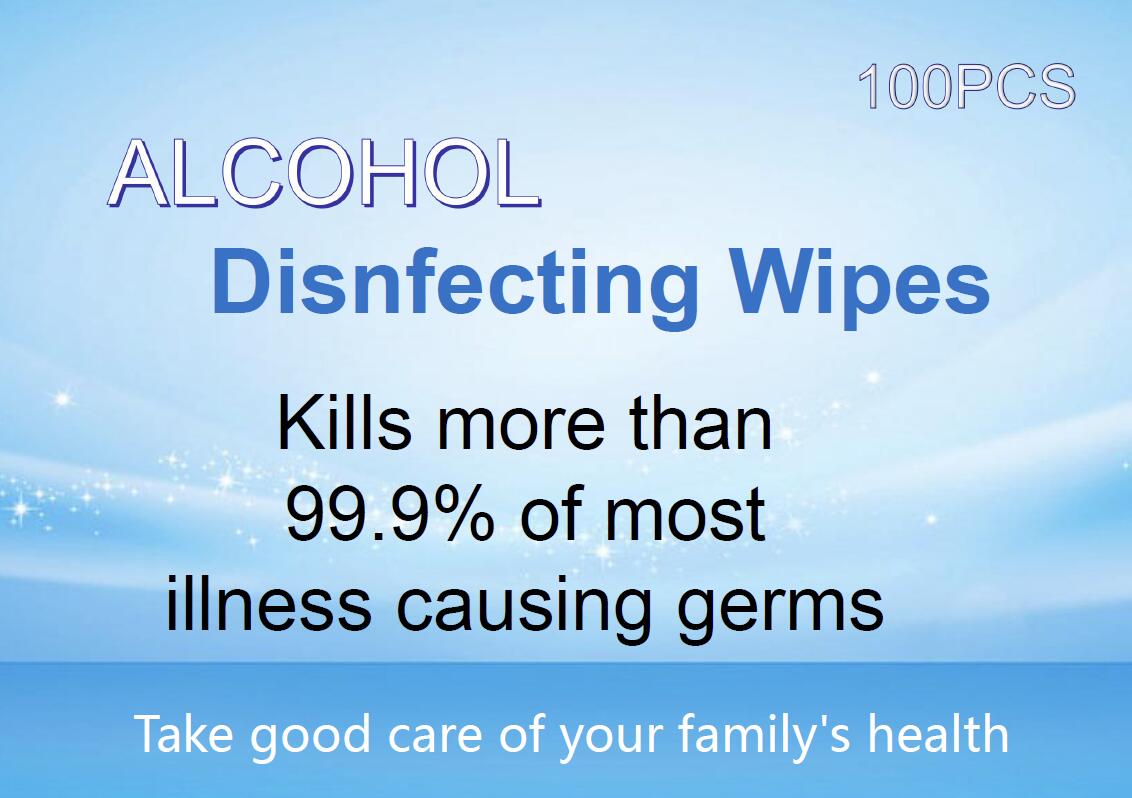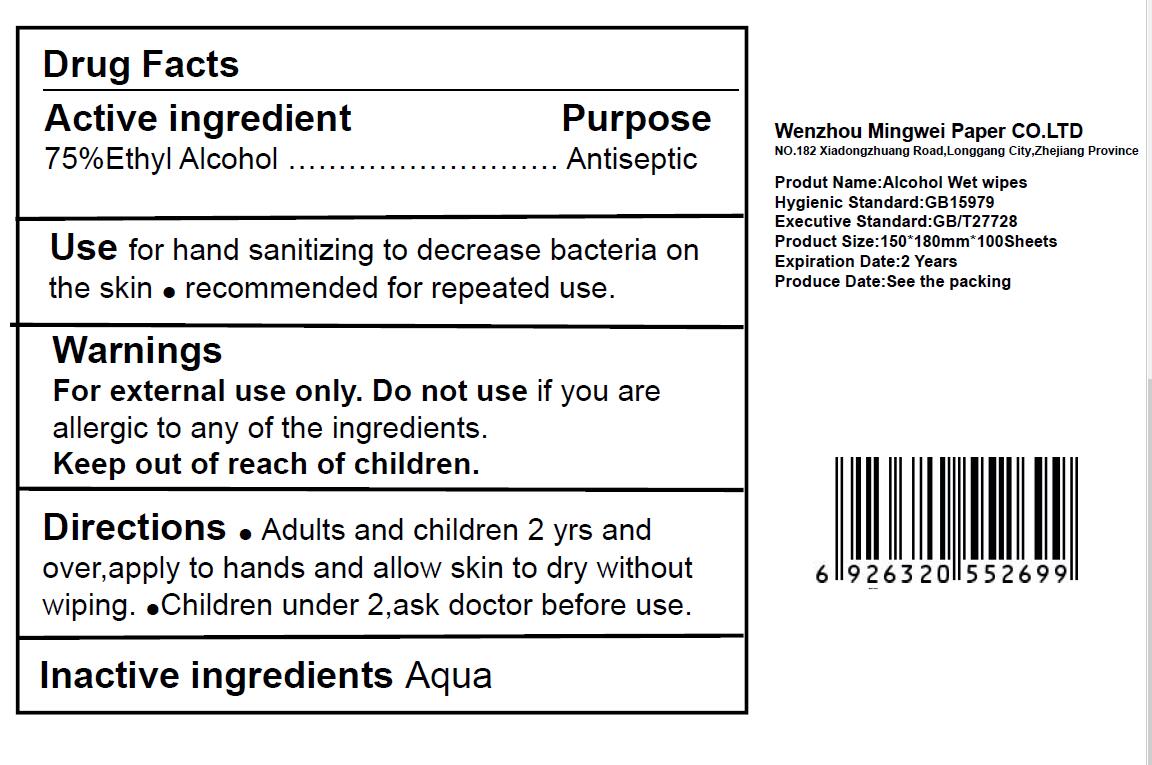 DRUG LABEL: Disnfecting Wipes
NDC: 78410-001 | Form: CLOTH
Manufacturer: Wenzhou Mingwei Paper  Co., Ltd.
Category: otc | Type: HUMAN OTC DRUG LABEL
Date: 20200913

ACTIVE INGREDIENTS: ALCOHOL 75 g/100 g
INACTIVE INGREDIENTS: WATER

78410-001 wet wipes 75% Ethyl Alcohol

Active Ingredient

Ethyl Alcohol 75%

USE

For hand washing to decrease bacteria on the skin.
Recommended for repeated use.

Warning

For external use only. Do not use if you are
allergic to any of the ingredients.

Keep out of reach of children.

Directions

● Adults and children 2 yrs and
over, apply to hands and allow skin to dry without
wiping.
Children under 2,ask doctor before use.

Inactive ingredients

Aqua

Purpose

Antiseptic